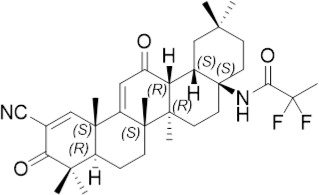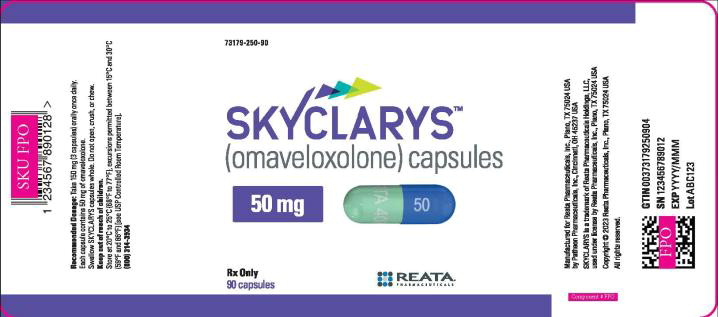 DRUG LABEL: SKYCLARYS
NDC: 64406-250 | Form: CAPSULE
Manufacturer: Biogen
Category: prescription | Type: HUMAN PRESCRIPTION DRUG LABEL
Date: 20241220

ACTIVE INGREDIENTS: omaveloxolone 50 mg/1 1
INACTIVE INGREDIENTS: croscarmellose sodium; magnesium stearate; starch, corn; microcrystalline cellulose; FD&C Blue No. 1; ferric oxide yellow; hypromellose, unspecified; titanium dioxide

HIGHLIGHTS OF PRESCRIBING INFORMATION

These highlights do not include all the information needed to use SKYCLARYS safely and effectively. See full prescribing information for SKYCLARYS.
SKYCLARYS® (omaveloxolone) capsules, for oral use
Initial U.S. Approval: 2023

RECENT MAJOR CHANGES

Dosage and Administration (2.2) | 12/2024

1 INDICATIONS AND USAGE

SKYCLARYS is indicated for the treatment of Friedreich's ataxia in adults and adolescents aged 16 years and older. (1)

2 DOSAGE AND ADMINISTRATION

- Obtain alanine aminotransferase (ALT), aspartate aminotransferase (AST), bilirubin, B-type natriuretic peptide (BNP), and lipid parameters prior to initiating SKYCLARYS and during treatment. (2.1, 5.1, 5.2, 5.3)
- Recommended dosage is 150 mg (3 capsules) taken orally once daily. (2.2)
- Administer SKYCLARYS on an empty stomach, at least 1 hour before or 2 hours after eating. (2.2)
- Swallow SKYCLARYS capsules whole or open and sprinkle the entire contents of both halves of the capsule onto applesauce and mix. Do not crush or chew capsules. (2.2)
- Moderate and Severe Hepatic Impairment: The recommended dosage of SKYCLARYS is 100 mg once daily for patients with moderate hepatic impairment. If adverse reactions emerge, further reduce the dosage to 50 mg once daily. Avoid use in patients with severe hepatic impairment. (2.5, 8.6, 12.3)

3 DOSAGE FORMS AND STRENGTHS

Capsules: 50 mg (3)

4 CONTRAINDICATIONS

None. (4)

5 WARNINGS AND PRECAUTIONS

- Elevation of Aminotransferases: Monitor ALT, AST, and total bilirubin prior to initiation, every month for the first 3 months of treatment, and periodically thereafter. (2.1, 5.1)
- Elevation of B-type Natriuretic Peptide (BNP): Advise patients of signs and symptoms of fluid overload. (2.1, 5.2)
- Lipid Abnormalities: Monitor cholesterol periodically during treatment. (2.1, 5.3)

6 ADVERSE REACTIONS

Most common adverse reactions (incidence ≥20% and greater than placebo) are elevated liver enzymes (AST/ALT), headache, nausea, abdominal pain, fatigue, diarrhea, and musculoskeletal pain. (6.1)

To report SUSPECTED ADVERSE REACTIONS, contact Biogen at 1-844-987-3224- or FDA at 1-800-FDA-1088 or www.fda.gov/medwatch.

7 DRUG INTERACTIONS

- Moderate or Strong CYP3A4 Inhibitors: Avoid concomitant use. Consider SKYCLARYS dosage reduction with monitoring if use is unavoidable. (2.4, 7.1)
- Moderate or Strong CYP3A4 Inducers: Avoid concomitant use. (7.1)

8 USE IN SPECIFIC POPULATIONS

Pregnancy: Based on animal data, may cause fetal harm. (8.1)

FULL PRESCRIBING INFORMATION

1 INDICATIONS AND USAGE

SKYCLARYS is indicated for the treatment of Friedreich's ataxia in adults and adolescents aged 16 years and older.

2 DOSAGE AND ADMINISTRATION

2.1 Recommended Testing Before Initiating SKYCLARYS and Monitoring to Assess Safety

Obtain ALT, AST, bilirubin, BNP, and lipid parameters prior to initiating SKYCLARYS and during treatment [see Warnings and Precautions (5.1, 5.2, 5.3)].

2.2 Recommended Dosage

The recommended dosage of SKYCLARYS is 150 mg (3 capsules) taken orally once daily.

- Administer SKYCLARYS on an empty stomach, at least 1 hour before or 2 hours after eating [see Clinical Pharmacology (12.3)].
- Swallow SKYCLARYS capsules whole. Do not crush or chew.
- For patients who are unable to swallow whole capsules:
  - SKYCLARYS capsules may be opened and the entire contents of both halves of the capsule sprinkled onto 2 tablespoons (30 mL) of applesauce [see Clinical Pharmacology (12.3)].
  - Stir the mixture until homogenous.
  - Swallow all the drug/applesauce mixture immediately.
  - Do not store the mixture for future use.
  - Contents of the SKYCLARYS capsules should not be mixed with milk or orange juice.
  - Not for enteral feeding tube administration.

2.3 Missed Doses

If a dose of SKYCLARYS is missed, take the next dose at its scheduled time the following day. A double dose should not be taken to make up for a missed dose.

2.4 Recommendations for Concomitant Use with Strong or Moderate CYP3A4 Inhibitors and Inducers

The recommended dosage for concomitant use of SKYCLARYS with cytochrome P450 (CYP) 3A4 inhibitors and inducers are described in Table 1 [see Drug Interactions (7.1) and Clinical Pharmacology (12.3)].

Table 1: Recommended Dosage of SKYCLARYS with Concomitant Use of CYP3A4 Inhibitors and Inducers
Concomitant Drug Class | Dosage
Strong CYP3A4 inhibitor | Recommended to avoid concomitant use. If coadministration cannot be avoided:; - Reduce the dosage of SKYCLARYS to 50 mg once daily with close monitoring for adverse reactions. - If adverse reactions emerge, coadministration with strong CYP3A4 inhibitors should be discontinued.
Moderate CYP3A4 inhibitor | Recommended to avoid concomitant use. If coadministration cannot be avoided:; - Reduce the dosage of SKYCLARYS to 100 mg once daily with close monitoring for adverse reactions. - If adverse reactions emerge, further reduce the dosage of SKYCLARYS to 50 mg once daily.
Strong or Moderate CYP3A4 inducer | Recommended to avoid concomitant use.

2.5 Recommended Dosage for Patients with Hepatic Impairment

The recommended dosage for patients with hepatic impairment are described in Table 2 [see Use in Specific Populations (8.6)].

Table 2: Recommended Dosage in Patients with Hepatic Impairment
Impairment Classification (Child-Pugh) | Dosage
Severe (Child-Pugh Class C) | Avoid use
Moderate (Child-Pugh Class B) | - 100 mg once daily with close monitoring for adverse reactions - Consider lowering to 50 mg once daily if adverse reactions emerge
Mild (Child-Pugh Class A) | 150 mg once daily

3 DOSAGE FORMS AND STRENGTHS

SKYCLARYS capsules contain 50 mg of omaveloxolone, and are supplied as opaque hard capsules having a light green body and blue cap, imprinted with “RTA 408” in white ink on the body and “50” in white ink on the cap.

4 CONTRAINDICATIONS

None.

5 WARNINGS AND PRECAUTIONS

5.1 Elevation of Aminotransferases

Treatment with SKYCLARYS can cause an elevation in hepatic transaminases (ALT and AST). In Study 1 [see Clinical Studies (14)], the incidence of elevations of ALT or AST above 5 times and 3 times the upper limit of normal (ULN) was 16% and 31%, respectively, in patients treated with SKYCLARYS. There were no cases of concomitant elevation of transaminases and total bilirubin observed in Study 1. Maximum increases in ALT and AST occurred within 12 weeks after starting SKYCLARYS. Increases in serum aminotransferases were generally asymptomatic and reversible following discontinuation of SKYCLARYS. Patients with clinically significant liver disease were excluded from Study 1.

Monitor ALT, AST, and total bilirubin prior to initiation of SKYCLARYS, every month for the first 3 months of treatment, and periodically thereafter. If transaminases increase to levels greater than 5 times the ULN, or greater than 3 times the ULN with evidence of liver dysfunction (e.g., elevated bilirubin), immediately discontinue SKYCLARYS and repeat liver function tests as soon as possible. If transaminase levels stabilize or resolve, SKYCLARYS may be reinitiated with an appropriate increased frequency of monitoring of liver function [see Adverse Reactions (6.1) and Use in Specific Populations (8.6)].

5.2 Elevation of B-Type Natriuretic Peptide

Treatment with SKYCLARYS can cause an increase in BNP, a marker of cardiac function. In Study 1, a total of 14% of patients treated with SKYCLARYS had an increase from baseline in BNP and a BNP above the ULN (100 pg/mL), compared to 4% of patients who received placebo. The incidence of elevation of BNP above 200 pg/mL was 4% in patients treated with SKYCLARYS. Cardiomyopathy and cardiac failure are common in patients with Friedreich's ataxia. Patients were excluded from Study 1 if they had BNP levels > 200 pg/mL prior to study entry, or a history of clinically significant left-sided heart disease and/or clinically significant cardiac disease, with the exception of mild to moderate cardiomyopathy associated with Friedreich's ataxia [see Adverse Reactions (6.1)]. Whether the elevations in BNP in Study 1 are related to SKYCLARYS or cardiac disease associated with Friedreich's ataxia is unclear.

Elevations in BNP may indicate cardiac failure and should prompt an evaluation of cardiac function. Check BNP prior to initiation of SKYCLARYS. Monitor patients for the signs and symptoms of fluid overload, such as sudden weight gain (3 pounds or more of weight gain in one day, or 5 pounds or more of weight gain in a week), peripheral edema, palpitations, and shortness of breath. If signs and symptoms of fluid overload develop, worsen, or require hospitalization, evaluate BNP and cardiac function, and manage appropriately. Management of fluid overload and heart failure may require discontinuation of SKYCLARYS.

5.3 Lipid Abnormalities

Treatment with SKYCLARYS can cause changes in cholesterol. In Study 1, 29% of patients treated with SKYCLARYS reported elevated cholesterol above ULN at one or more time points. Mean increases were observed within 2 weeks of initiation of SKYCLARYS and returned to baseline within 4 weeks of discontinuing treatment. A total of 16% of patients treated with SKYCLARYS had an increase in low-density lipoprotein cholesterol (LDL-C) from baseline, compared to 8% of patients who received placebo. The mean increase in LDL-C for all SKYCLARYS-treated patients was 23.5 mg/dL at 48 weeks. A total of 6% of patients treated with SKYCLARYS had decreases in high-density lipoprotein cholesterol (HDL-C) from baseline compared to 4% of patients who received placebo. The mean decrease in HDL-C for all SKYCLARYS-treated patients was 5.3 mg/dL at 48 weeks.

Assess lipid parameters prior to initiation of SKYCLARYS and monitor periodically during treatment. Manage lipid abnormalities according to clinical guidelines.

6 ADVERSE REACTIONS

The following clinically significant adverse reactions are described in greater detail in other labeling sections:

- Elevation of aminotransferases [see Warnings and Precautions (5.1)]
- Elevation of BNP [see Warnings and Precautions (5.2)]
- Lipid abnormalities [see Warnings and Precautions (5.3)]

6.1 Clinical Trials Experience

Because clinical trials are conducted under widely varying conditions, adverse reaction rates observed in the clinical trials of a drug cannot be directly compared with rates in clinical trials of another drug and may not reflect the rates observed in clinical practice.

The safety of SKYCLARYS 150 mg once daily has been evaluated in 165 patients with Friedreich's ataxia, including 137 patients exposed for at least 48 weeks, and 125 patients exposed for at least 96 weeks.

The most common adverse reactions in Study 1 (≥20% and greater than placebo) were elevated liver enzymes (AST/ALT), headache, nausea, abdominal pain, fatigue, diarrhea, and musculoskeletal pain. Table 3 shows the adverse reactions that occurred in 10% or more of patients treated with SKYCLARYS and greater than placebo.

Table 3: Adverse Reactions Reported in 10% or More of Patients Treated with SKYCLARYS and Greater than Placebo (Study 1)
Adverse Reactions | SKYCLARYS 150 mg (N = 51) % | Placebo (N = 52) %
Elevated liver enzymes (AST/ALT) | 37 | 2
Headache | 37 | 25
Nausea | 33 | 13
Abdominal pain | 29 | 6
Fatigue | 24 | 14
Diarrhea | 20 | 10
Musculoskeletal pain | 20 | 15
Oropharyngeal pain | 18 | 6
Influenza | 16 | 6
Vomiting | 16 | 12
Muscle spasms | 14 | 6
Back pain | 13 | 8
Decreased appetite | 12 | 4
Rash | 10 | 4

Laboratory Abnormalities

In addition to elevated liver enzymes, additional laboratory abnormalities include elevation of BNP and lipid abnormalities [see Warnings and Precautions (5.1, 5.2, 5.3)].

6.2 Postmarketing Experience

The following adverse reactions have been identified during post approval use of SKYCLARYS. Because these reactions are reported voluntarily from a population of uncertain size, it is not always possible to reliably estimate their frequency or establish a causal relationship to drug exposure.

Immune System Disorders: hypersensitivity (urticaria, rash)

7 DRUG INTERACTIONS

7.1 Effect of Other Drugs on SKYCLARYS

CYP3A4 Inhibitors

Omaveloxolone is a CYP3A4 substrate. Concomitant use of SKYCLARYS with moderate or strong CYP3A4 inhibitors is expected to result in clinically significant increased exposure of omaveloxolone [see Clinical Pharmacology (12.3)], which may increase the risk of adverse reactions. Avoid concomitant use of SKYCLARYS with moderate or strong CYP3A4 inhibitors. If use cannot be avoided, dosage modifications are recommended [see Dosage and Administration (2.4)].

CYP3A4 Inducers

Omaveloxolone is a CYP3A4 substrate. Concomitant use of SKYCLARYS with moderate or strong CYP3A4 inducers is expected to result in clinically significant decreased exposure of omaveloxolone [see Clinical Pharmacology (12.3)], which may reduce the effectiveness of SKYCLARYS. Avoid concomitant use of SKYCLARYS with moderate or strong CYP3A4 inducers.

7.2 Effect of SKYCLARYS on Other Drugs

CYP3A4 and CYP2C8 Substrates

Omaveloxolone is a weak inducer of CYP3A4 and CYP2C8. Concomitant use with SKYCLARYS can reduce the exposure of CYP3A4 and CYP2C8 substrates which may reduce the activity of these substrates [see Clinical Pharmacology (12.3)]. Refer to the prescribing information of substrates of CYP3A4 and CYP2C8 for dosing instructions if used concomitantly with SKYCLARYS and monitor for lack of efficacy of the concomitant treatment.

Hormonal Contraceptives

Omaveloxolone is a weak CYP3A4 inducer [see Clinical Pharmacology (12.3)]. Concomitant use with SKYCLARYS may reduce the efficacy of hormonal contraceptives. Advise patients to avoid concomitant use with combined hormonal contraceptives (e.g., pill, patch, ring), implants, and progestin only pills [see Use in Specific Populations (8.3)].

8 USE IN SPECIFIC POPULATIONS

8.1 Pregnancy

Pregnancy Exposure Registry

There is a pregnancy exposure registry that monitors pregnancy outcomes in women exposed to SKYCLARYS during pregnancy. Healthcare providers are encouraged to enroll pregnant patients, or pregnant women may register themselves in the program by calling 1-866-609-1785 or by sending an email to SkyclarysPregnancySurveillance@ppd.com.

Risk Summary

There are no adequate data on the developmental risks associated with the use of SKYCLARYS in pregnant women. In animal studies, administration of omaveloxolone during pregnancy or throughout pregnancy and lactation produced evidence of developmental toxicity (embryofetal mortality and growth impairment, and mortality, growth impairment, and neurobehavioral deficits in offspring) at plasma exposures similar to or less than exposures in humans (see Animal Data). In the U.S. general population, the estimated background risk of major birth defects and miscarriage in clinically recognized pregnancies is 2% to 4% and 15% to 20%, respectively. The background risk of major birth defects and miscarriage for the indicated population is unknown.

Data

Animal Data

Oral administration of omaveloxolone (0, 1, 3, or 10 mg/kg/day) to pregnant rats throughout organogenesis resulted in no adverse effects on embryofetal development; however, in a dose range-finding study, oral administration of omaveloxolone at doses up to 30 mg/kg/day to pregnant rats throughout organogenesis produced increases in post-implantation loss and resorptions, resulting in a decrease in viable fetuses, and reduced fetal weight at the highest dose tested. At the highest dose tested in the pivotal study (10 mg/kg/day), plasma exposure (AUC) was approximately 5 times that in humans at the recommended human dose (RHD) of 150 mg/day.

Oral administration of omaveloxolone (0, 3, 10, or 30 mg/kg/day) to pregnant rabbits throughout organogenesis resulted in increased embryofetal mortality and skeletal variations and reduced fetal weight at the highest dose tested, which was associated with maternal toxicity. At the no-effect dose for adverse effects on embryofetal development (10 mg/kg/day), plasma exposure was less than that in humans at the RHD.

Oral administration of omaveloxolone (0, 1, 3, or 10 mg/kg/day) to rats throughout pregnancy and lactation resulted in an increase in stillbirths and impaired neurobehavioral function (increased locomotor activity and learning and memory deficits) in offspring at all doses, reduced body weight in offspring at all but the lowest dose tested, and delayed sexual maturation (males), increased postnatal mortality, and impaired reproductive performance in offspring at the highest dose tested. A no-effect dose for adverse effects on pre- and postnatal development was not identified. Plasma exposure (AUC) at the lowest dose tested was less than that in humans at the RHD.

8.2 Lactation

Risk Summary

There are no data on the presence of omaveloxolone or its metabolites in human milk. The effects on milk production and the breastfed infant are unknown. Omaveloxolone was excreted in the milk of lactating rats following oral administration. The developmental and health benefits of breastfeeding should be considered along with the mother's clinical need for SKYCLARYS and any potential adverse effects on the breastfed infant from SKYCLARYS or from the underlying maternal condition.

8.3 Females and Males of Reproductive Potential

SKYCLARYS may decrease the efficacy of hormonal contraceptives [see Drug Interactions (7.2) and Clinical Pharmacology (12.3)]. Advise patients to avoid concomitant use with combined hormonal contraceptives (e.g., pill, patch, ring), implants, and progestin only pills. Counsel females using hormonal contraceptives to use an alternative contraceptive method (e.g., non-hormonal intrauterine system) or additional non-hormonal contraceptive (e.g., condoms) during concomitant use and for 28 days after discontinuation of SKYCLARYS.

8.4 Pediatric Use

The safety and effectiveness of SKYCLARYS for the treatment of Friedreich's ataxia have been established in pediatric patients aged 16 years and older. Use of SKYCLARYS for this indication is supported by evidence from one adequate and well-controlled study (Study 1) in adults and in pediatric patients aged 16 years and older [see Clinical Studies (14)].

Safety and effectiveness of SKYCLARYS have not been established in pediatric patients less than 16 years of age.

8.5 Geriatric Use

Clinical studies of SKYCLARYS in Friedreich's ataxia did not include patients aged 65 and over. No data are available to determine whether they respond differently than younger adult patients.

8.6 Hepatic Impairment

Omaveloxolone plasma exposure is increased in patients with moderate or severe hepatic impairment (Child-Pugh Class B and C) [see Clinical Pharmacology (12.3)]. Avoid treatment with SKYCLARYS in patients with severe hepatic impairment, including those who develop severe hepatic impairment. If hepatic function improves to moderate impairment, mild impairment, or normal function, initiation of SKYCLARYS treatment at the approved recommended dosage may be considered. For patients with moderate hepatic impairment, a reduced dosage is recommended with close monitoring for adverse reactions [see Dosage and Administration (2.5)]. For patients with mild hepatic impairment (Child-Pugh Class A), no dose adjustments are recommended.

11 DESCRIPTION

SKYCLARYS contains omaveloxolone in immediate release capsules for oral administration available in a 50 mg strength. The chemical name of omaveloxolone is N-(2-cyano-3,12-dioxo-28-noroleana-1,9(11)-dien-17-yl)-2,2-difluoro-propanamide. Omaveloxolone is a white to off-white amorphous solid. The molecular formula is C33H44F2N2O3. Molecular weight is 554.72 g/mol. The chemical structure is:

Omaveloxolone has a pKa of 7.26 and is practically insoluble in water across the physiological pH range. Capsule contents include the following inactive ingredients: croscarmellose sodium, magnesium stearate, pregelatinized starch, and silicified microcrystalline cellulose. The hard capsule shells contain FD&C Blue #1, ferric oxide yellow, hypromellose, titanium dioxide, and white ink.

12 CLINICAL PHARMACOLOGY

12.1 Mechanism of Action

The precise mechanism by which omaveloxolone exerts its therapeutic effect in patients with Friedreich's ataxia is unknown. Omaveloxolone has been shown to activate the Nuclear factor (erythroid-derived 2)-like 2 (Nrf2) pathway in vitro and in vivo in animals and humans. The Nrf2 pathway is involved in the cellular response to oxidative stress.

12.2 Pharmacodynamics

Cardiac Electrophysiology

Clinically significant QTc interval prolongation was not observed in healthy subjects with administration of SKYCLARYS at a supratherapeutic dose of 450 mg (3 times the recommended dosage) with a high fat meal.

12.3 Pharmacokinetics

Absorption

The median (range) time to achieve peak plasma concentration (Tmax) was 7 to 14 (1 to 24) hours. The total plasma omaveloxolone exposure based on area under the concentration-time curve (AUC) increased in a dose-dependent and dose proportional manner over a dose range of 50 mg (0.33 times the recommended dosage) to 150 mg, but maximum omaveloxolone plasma concentration (Cmax) increased in a less than dose proportional manner over the dose range in healthy fasted subjects.

Effect of Food

Omaveloxolone Cmax and AUC0-inf increased by approximately 350% and 15%, respectively, with a high-fat meal (800-1000 calories, approximately 150, 250, and 500 to 600 calories from protein, carbohydrate, and fat, respectively) compared to fasted conditions [see Dosage and Administration (2.2)].

Omaveloxolone Cmax and AUC0-inf were similar when capsule contents were sprinkled on applesauce or when administered as intact capsules. The median Tmax of omaveloxolone was shortened from approximately 10 to 6 hours when sprinkled on applesauce [see Dosage and Administration (2.2)].

Distribution

The mean apparent volume of distribution of omaveloxolone is 7361 L (105 L/kg for a 70 kg person). Protein binding of omaveloxolone is 97%.

Elimination

The mean (range) terminal half-life of omaveloxolone is 57 hours (32 to 90 hours). The mean apparent plasma clearance of omaveloxolone is 109 L/hr.

Metabolism

Omaveloxolone is primarily metabolized by CYP3A with minor metabolism by CYP2C8 and CYP2J2.

Excretion

Following administration of a single oral dose of radiolabeled omaveloxolone 150 mg to healthy subjects, approximately 92% of the dose was recovered in feces (approximately 91% within 96 hours after administration) and 0.1% in urine.

Specific Populations

There were no clinically significant differences in the pharmacokinetics of omaveloxolone based on age (16 to 71 years of age), sex, race, or body weight (41 to 128 kg).

Patients with Renal Impairment

Population pharmacokinetic analysis demonstrated that estimated glomerular filtration rate (eGFR) values ≥ 63 mL/min/1.73 m^2 did not have a significant effect on the pharmacokinetics of omaveloxolone. Therefore, mild renal impairment (eGFR ≥60 to <90 mL/min/1.73 m^2) is not expected to have a significant effect on the pharmacokinetics of omaveloxolone. The effect of moderate or severe renal impairment (eGFR ≤59 mL/min/1.73m^2) on the pharmacokinetics of omaveloxolone is unknown.

Patients with Hepatic Impairment

There were no clinically significant differences in the pharmacokinetics of omaveloxolone in subjects with mild hepatic impairment (Child-Pugh Class A). In subjects with moderate and severe hepatic impairment (Child-Pugh Class B and C), omaveloxolone clearance was reduced, resulting in higher plasma exposure of omaveloxolone. The omaveloxolone AUC increased up to 1.65-fold and Cmax increased up to 1.83-fold in subjects with moderate hepatic impairment. The omaveloxolone AUC increased up to 2.17-fold in subjects with severe hepatic impairment; however, this change was variable [see Use in Specific Populations (8.6)].

Drug Interaction Studies

Clinical Studies

Strong CYP3A Inhibitors: After single dose administration, omaveloxolone Cmax increased 3-fold and AUC 4-fold following concomitant use with itraconazole (strong CYP3A inhibitor) [see Drug Interactions (7.1)].

Moderate CYP3A Inhibitors: After single dose administration, omaveloxolone Cmax and AUC increased approximately 1.25-fold following concomitant use with verapamil (moderate CYP3A4 and P-gp inhibitor) [see Drug Interactions (7.1)].

Moderate CYP3A Inducers: After single dose administration, omaveloxolone Cmax and AUC decreased 38% and 48%, respectively, following concomitant use with efavirenz (moderate CYP3A4 inducer) [see Drug Interactions (7.1)].

Certain CYP450 Enzymes or Transporter Substrates: Omaveloxolone decreased the AUC of midazolam (CYP3A4 substrate) by approximately 45%, AUC of repaglinide (CYP2C8 substrate) by approximately 35%, and AUC of rosuvastatin (BCRP and OATP1B1 substrate) by approximately 30% [see Drug Interactions (7.2)]. There were no clinically significant differences in the pharmacokinetics of digoxin (P-gp substrate) or metformin [(organic cation transporter (OCT)1 substrate] when co-administered with omaveloxolone.

Other Drugs: No clinically significant differences in the pharmacokinetics of omaveloxolone are expected following concomitant use with weak CYP3A4 inhibitors or strong CYP2C8 inhibitors.

In Vitro Studies

CYP Enzymes: Omaveloxolone is an inducer of CYP3A4 and CYP2C19. Omaveloxolone is not an inhibitor of CYP1A2, CYP2B6, CYP2C9, CYP2C19, and CYP2D6. Omaveloxolone is not an inducer of CYP1A2, CYP2B6, CYP2C8, and CYP2C9.

Drug Transporters: Omaveloxolone is not an inhibitor of BCRP, BSEP, OAT3, OATP1B1, OATP1B3, OCT2, MATE1, and MATE2-K. Omaveloxolone inhibited the renal transporter OAT1.

13 NONCLINICAL TOXICOLOGY

13.1 Carcinogenesis, Mutagenesis, Impairment of Fertility

Carcinogenesis

In a 26-week carcinogenicity study in transgenic (Tg.rasH2) mice, oral administration of omaveloxolone (0, 5, 10, or 30 mg/kg/day in males; 0, 20, 50, or 100 mg/kg/day in females) resulted in no increase in tumors.

Mutagenesis

Omaveloxolone was negative in a bacterial reverse mutation (Ames) assay, and positive in a chromosomal aberration assay in human peripheral blood lymphocytes but negative in the in vivo rat micronucleus assay and the in vitro comet assay.

Impairment of Fertility

Oral administration of omaveloxolone (0, 1, 3, and 10 mg/kg/day) to male and female rats prior to and during mating and continuing in females to gestation day 7 produced an increase in pre-and post-implantation loss and resorptions, resulting in a decrease in viable embryos at the highest dose tested. The no-effect dose (3 mg/kg/day) for adverse effects on fertility and reproductive function was associated with plasma exposures (AUC) approximately 2 times that in humans at the recommended human dose of 150 mg/day.

14 CLINICAL STUDIES

The efficacy of SKYCLARYS was evaluated in a 48-week, randomized, double-blind, placebo-controlled study in patients 16 to 40 years of age with Friedreich's Ataxia (Study 1; NCT02255435).

A total of 103 patients were randomized (1:1) to receive SKYCLARYS 150 mg once daily (n=51) or placebo (n=52).

Enrolled patients had to have a stable modified Friedreich's Ataxia Rating Scale (mFARS) score between 20 and 80, be able to complete maximal exercise testing, and have a left ventricular ejection fraction of at least 40%. In Study 1, 53% of enrolled patients were male, 97% were White, and the mean age was 24 years at study entry. Patients with or without pes cavus were included in Study 1. Pes cavus was defined as having a loss of lateral support and was determined if light from a flashlight could be seen under the patient's arch when barefoot and weight bearing.

The prespecified primary analysis was the change from baseline in the mFARS score compared to placebo at Week 48 in the Full Analysis Population of patients without pes cavus (n=82). The mFARS is a clinical assessment tool to assess patient function, which consists of 4 domains to evaluate bulbar function, upper limb coordination, lower limb coordination, and upright stability. The mFARS has a maximum score of 99, with a lower score on the mFARS signifying lesser physical impairment.

Treatment with SKYCLARYS resulted in statistically significant lower mFARS scores (less impairment) relative to placebo (see Table 4) at Week 48.

Table 4: Primary Analysis in Full Analysis Population: mFARS Least Squares (LS) Mean Change from Baseline at Week 48
 | Mean (SD) Baseline mFARS Total Score | LS Mean Change from Baseline at Week 48 | Treatment difference SKYCLARYS-placebo (95% CI) | p-value
SKYCLARYS (n = 40) | 40.95 (10.39) | -1.56 | -2.41 (-4.32, -0.51) | 0.0138
Placebo (n = 42) | 38.78 (11.03) | 0.85 | -2.41 (-4.32, -0.51) | 0.0138
SD = Standard Deviation; LS = Least Squares; CI = Confidence Interval

The All Randomized Population (N=103), which included all patients regardless of pes cavus status, demonstrated similar results to the Full Analysis Population of lower mFARS scores in patients treated with SKYCLARYS compared to placebo, with a nominally significant least squares mean difference between treatment groups of ‑1.94 (95% CI: -3.71, -0.16, p=0.0331).

In a post hoc, propensity-matched analysis, lower mFARS scores were observed in patients treated with SKYCLARYS after 3 years relative to a matched set of untreated patients from a natural history study. These exploratory analyses should be interpreted cautiously given the limitations of data collected outside of a controlled study, which may be subject to confounding.

16 HOW SUPPLIED/STORAGE AND HANDLING

16.1 How Supplied

SKYCLARYS (omaveloxolone) capsules, 50 mg, are supplied as opaque, hard capsules having a light green body and blue cap imprinted with “RTA 408” in white ink on the body and “50” in white ink on the cap. SKYCLARYS is supplied in high density polyethylene bottles that contain 90 capsules, with a foil induction seal and child-resistant closure (NDC 64406-250-90).

16.2 Storage and Handling

Store at 20°C to 25°C (68°F to 77°F), excursions permitted between 15°C and 30°C (59°F to 86°F) [see USP Controlled Room Temperature].

17 PATIENT COUNSELING INFORMATION

Advise the patient to read the FDA-approved patient labeling (Patient Information).

Elevation of Aminotransferases

Inform patients that elevation in aminotransferases have occurred in patients treated with SKYCLARYS. Liver function tests will be performed prior to initiating SKYCLARYS, every month for the first 3 months of treatment, and periodically thereafter as needed [see Warnings and Precautions (5.1)].

Fluid Overload

Inform patients that elevations in BNP, a marker of cardiac function, have occurred in patients treated with SKYCLARYS. BNP will be performed prior to initiating SKYCLARYS and if signs and symptoms of fluid overload occur, such as sudden weight gain, peripheral edema, palpitations, and shortness of breath. Advise patients to contact their healthcare provider if signs and symptoms of fluid overload develop [see Warnings and Precautions (5.2)].

Lipid Abnormalities

Inform patients that treatment with SKYCLARYS has been associated with increases in LDL cholesterol and decreases in HDL cholesterol. Cholesterol will be assessed prior to starting SKYCLARYS and monitored periodically during treatment [see Warnings and Precautions (5.3)].

Drug Interactions

Advise patients to discuss all medications they are taking, including other prescription medications, non-prescription medications, or herbal products (e.g., St. John's Wort) with their healthcare provider [see Drug Interactions (7)].

Pregnancy

Advise women to notify their healthcare provider if they become pregnant or intend to become pregnant during SKYCLARYS therapy. Inform patients that there is a pregnancy exposure registry that monitors pregnancy outcomes in women exposed to SKYCLARYS during pregnancy [see Use in Specific Populations (8.1)].

Females of Reproductive Potential

Counsel females using hormonal contraceptives to use an alternative contraceptive method (e.g., non-hormonal intrauterine system) or additional non-hormonal contraceptive (e.g., condoms) during concomitant use and for 28 days after discontinuation of SKYCLARYS [see Drug Interactions (7.2) and Use in Specific Populations (8.3)].

Administration

Advise patients to take SKYCLARYS on an empty stomach, at least 1 hour before or 2 hours after eating [see Dosage and Administration (2.2)].

Advise patients to swallow SKYCLARYS capsules whole or to open the capsules and sprinkle the entire contents of both halves onto 2 tablespoons (30 mL) of applesauce, then stir the mixture. If sprinkled, advise patients to swallow the drug/applesauce mixture immediately and not to store for future use. Do not crush or chew the capsules. Inform patients that the contents of the SKYCLARYS capsules should not be mixed with milk or orange juice. Advise patients to not administer SKYCLARYS by an enteral feeding tube [see Dosage and Administration (2.2)].

Advise patients that if a dose of SKYCLARYS is missed to not to double their dose or take more than the prescribed dose [see Dosage and Administration (2.3)].

Advise patients to avoid grapefruit juice and grapefruit while they are taking SKYCLARYS [see Drug Interactions (7.1)].

59564-03

Manufactured for Biogen U.S. Corporation, Cambridge, MA

© Biogen 2024
All rights reserved

PATIENT INFORMATION
SKYCLARYS® (skye klar' is)
(omaveloxolone)
capsules, for oral use

What is SKYCLARYS?
SKYCLARYS is used for the treatment of Friedreich's ataxia in adults and children aged 16 years and older.
It is not known if SKYCLARYS is safe and effective for use in children younger than 16 years of age.

Before taking SKYCLARYS, tell your healthcare provider about all of your medical conditions, including if you:

- have liver problems.
- have a history of heart problems, including heart failure.
- have a high level of fat in your blood (high blood cholesterol).
- are pregnant or plan to become pregnant.
  - It is not known if SKYCLARYS will harm your unborn baby.
  - Women who use hormonal birth control should use another form of birth control such as a non-hormonal intrauterine system or an extra non-hormonal birth control such as condoms while using SKYCLARYS and for 28 days after stopping SKYCLARYS.
  - Pregnancy exposure registry: There is a pregnancy registry for women who are pregnant and are taking SKYCLARYS. The purpose of this registry is to collect information about the health of you and your baby. Your healthcare provider can enroll you or you may enroll yourself by calling 1-866-609-1785 or by sending an email to SkyclarysPregnancySurveillance@ppd.com.
- are breastfeeding or plan to breastfeed. It is not known if SKYCLARYS passes into your breast milk. Talk to your healthcare provider about the best way to feed your baby if you take SKYCLARYS.

Tell your healthcare provider about all the medicines you take, including prescription and over-the-counter medicines, vitamins, and herbal supplements such as St. John's Wort.
Taking SKYCLARYS with other medicines can cause serious side effects.
SKYCLARYS may affect the way other medicines work, and other medicines may affect how SKYCLARYS works.
Know the medicines you take. Keep a list of them to show to your healthcare provider and pharmacist when you get a new medicine.

How should I take SKYCLARYS?

- Take SKYCLARYS exactly as your healthcare provider tells you to take it.
- Take SKYCLARYS capsules on an empty stomach, at least 1 hour before or 2 hours after eating.
- Swallow SKYCLARYS capsules whole. Do not crush or chew.
- If SKYCLARYS capsules cannot be swallowed whole, the capsules may be opened and the entire contents of both halves sprinkled onto 2 tablespoonfuls (30 mL) of applesauce.
  - Stir the mixture.
  - Swallow all the mixture of medicine and applesauce right away. Do not store the mixture of medicine and applesauce to use at a later time.
  - The contents of the SKYCLARYS capsules should not be mixed with milk or orange juice.
  - Do not administer SKYCLARYS by an enteral feeding tube.
- If you miss a dose, then you should skip the missed dose and take the next dose at the regular time the next day. Do not double your next dose or take more than the prescribed dose.

What should I avoid while taking SKYCLARYS?
Do not drink grapefruit juice or eat grapefruit. These may change the amount of SKYCLARYS in your blood.

What are the possible side effects of SKYCLARYS?
SKYCLARYS may cause serious side effects, including:

- increase in blood liver enzymes. Some people taking SKYCLARYS have had an increase in the level of liver enzymes in their blood. Your healthcare provider will do liver function tests
  - before you start taking SKYCLARYS
  - every month for the first 3 months after starting your treatment with SKYCLARYS
  - during certain times as needed while taking SKYCLARYS

If your liver enzymes increase, your healthcare provider may change your dose during treatment, stop treatment for some time, or completely stop treatment with SKYCLARYS.

- increase in a blood protein called B-Type Natriuretic Peptide (BNP). BNP tells how well your heart is working. Your healthcare provider will check your BNP levels before your treatment with SKYCLARYS. Tell your healthcare provider if you have signs and symptoms of your heart not working well such as too much fluid in your body (fluid overload). Signs and symptoms may include:
  - sudden weight gain (3 pounds or more of weight gain in 1 day, or 5 pounds or more of weight gain in 1 week)
  - swelling in your arms, hands, legs, or feet (peripheral edema)
  - fast heartbeat (palpitations)
  - shortness of breath

If you have symptoms of fluid overload that is considered a side effect of SKYCLARYS, your healthcare provider may stop treatment with SKYCLARYS.

- changes in cholesterol levels. Increases in low density lipoprotein cholesterol (LDL-C) or bad cholesterol and decreases in high density lipoprotein cholesterol (HDL-C) or good cholesterol have happened during treatment with SKYCLARYS.
  Your healthcare provider will check your cholesterol levels before and during your treatment with SKYCLARYS.

The most common side effects of SKYCLARYS include:

- increased liver enzymes (ALT/AST)
- headache
- nausea
- stomach pain
- tiredness
- diarrhea
- muscle pain

These are not all the possible side effects of SKYCLARYS.
Call your doctor for medical advice about side effects. You may report side effects to FDA at 1-800-FDA-1088.

How should I store SKYCLARYS?

- Store SKYCLARYS at room temperature between 68°F to 77°F (20°C to 25°C)

Keep SKYCLARYS and all medicines out of the reach of children.

General information about the safe and effective use of SKYCLARYS.
Medicines are sometimes prescribed for purposes other than those listed in a Patient Information leaflet. Do not use SKYCLARYS for a condition for which it was not prescribed. Do not give SKYCLARYS to other people, even if they have the same symptoms you have. It may harm them. You can ask your healthcare provider or pharmacist for information about SKYCLARYS that is written for health professionals.

What are the ingredients in SKYCLARYS?
Active ingredient: omaveloxolone
Inactive ingredients: croscarmellose sodium, magnesium stearate, pregelatinized starch, silicified microcrystalline cellulose. The hard capsule shells contain FD&C Blue #1, ferric oxide yellow, hypromellose, titanium dioxide, and white edible ink.
Manufactured for Biogen U.S. Corporation, Cambridge, MA
© Biogen 2024
All rights reserved
For more information about SKYCLARYS®, go to www.SKYCLARYS.com or call Biogen.at 1-844-987-3224.

This Patient Information has been approved by the U.S. Food and Drug Administration Approved: 12/2024

PRINCIPAL DISPLAY PANEL

73179-250-90
SKYCLARYS
(omaveloxolone)
50 mg capsules
Rx only
90 capsules